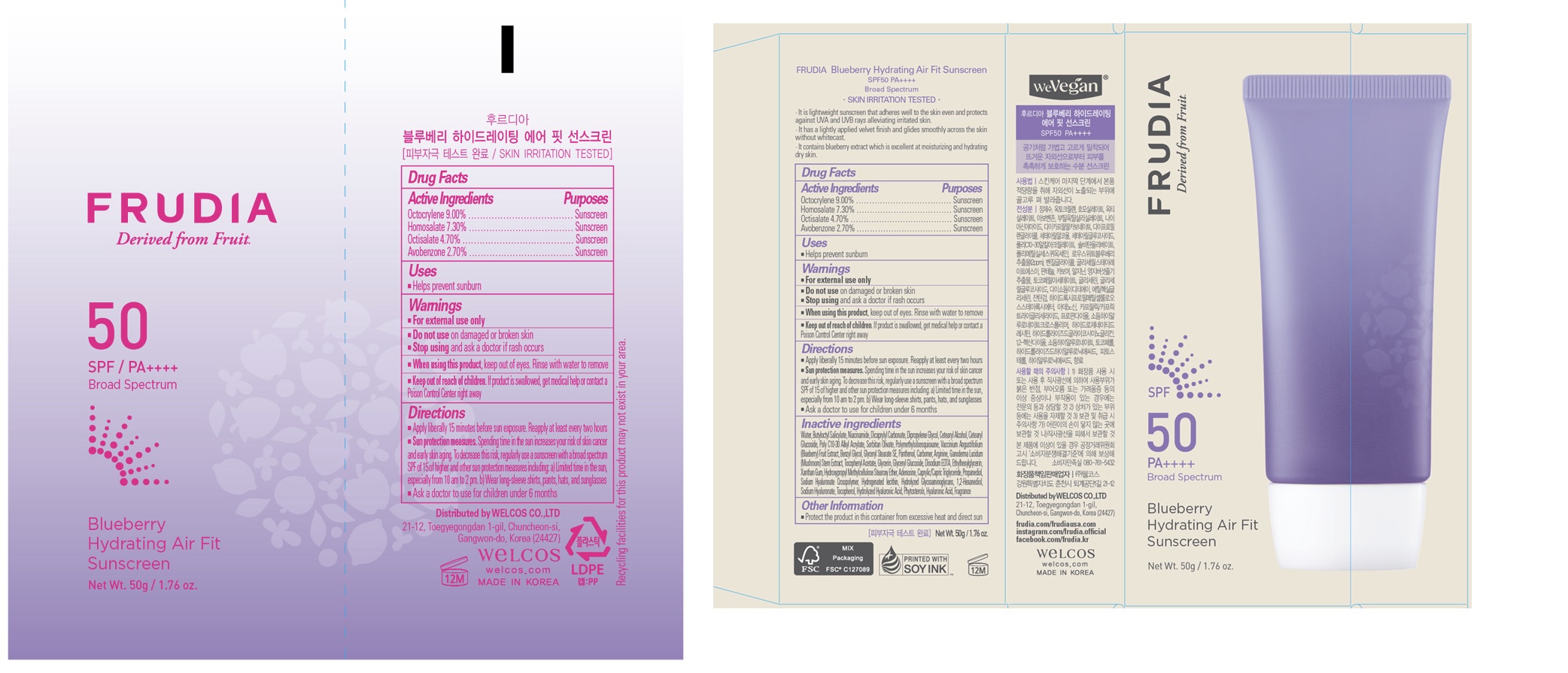 DRUG LABEL: FRUDIA Blueberry Hydrating Air Fit Sunscreen
NDC: 71017-001 | Form: CREAM
Manufacturer: WELCOS CO.,LTD.
Category: otc | Type: HUMAN OTC DRUG LABEL
Date: 20250228

ACTIVE INGREDIENTS: OCTOCRYLENE 90 mg/1 g; HOMOSALATE 73 mg/1 g; OCTISALATE 47 mg/1 g; AVOBENZONE 27 mg/1 g
INACTIVE INGREDIENTS: WATER; BUTYLOCTYL SALICYLATE; NIACINAMIDE; DICAPRYLYL CARBONATE; DIPROPYLENE GLYCOL; CETEARYL GLUCOSIDE; BEHENYL ACRYLATE POLYMER; SORBITAN OLIVATE; POLYMETHYLSILSESQUIOXANE (4.5 MICRONS); LOWBUSH BLUEBERRY; ETHYLENE GLYCOL MONOBENZYL ETHER; GLYCERYL STEARATE SE; PANTHENOL; CARBOMER HOMOPOLYMER, UNSPECIFIED TYPE; ARGININE; GANODERMA LUCIDUM STEM; .ALPHA.-TOCOPHEROL ACETATE; GLYCERIN; GLYCERYL GLUCOSIDE; EDETATE DISODIUM; ETHYLHEXYLGLYCERIN; XANTHAN GUM; HYPROMELLOSE 2208 0.45% STEAROXY ETHER; ADENOSINE; MEDIUM-CHAIN TRIGLYCERIDES; PROPANEDIOL; HYDROGENATED SOYBEAN LECITHIN; HYDROLYZED GLYCOSAMINOGLYCANS (BOVINE; 50000 MW); 1,2-HEXANEDIOL; HYALURONATE SODIUM; TOCOPHEROL; HYALURONIC ACID; CETOSTEARYL ALCOHOL

71017-001_FRUDIA Blueberry Hydrating Air Fit Sunscreen

DOSAGE AND ADMINISTRATION

- Apply liberally 15 minutes before sun exposure. Reapply at least every two hours
- Sun protection measures. Spending time in the sun increases your risk of skin cancer and early skin aging. To decrease this risk, regularly use a sunscreen with a broad spectrum SPF of 15 of higher and other sun protection measures including: 1) Limited time in the sun, especially from 10 am to 2 pm. 2) Wear long-sleeve shirts, pants, hats, and sunglasses
- Ask a doctor to use for children under 6 months

ACTIVE INGREDIENT

Octocrylene 9.00%

Homosalate 7.30%

Octisalate 4.70%

Avobenzone 2.70%

PURPOSE

Sunscreen

INDICATIONS AND USAGE

Helps prevent sunburn

WARNINGS

For external use only

Do not use on damaged or broken skin

Stop using and ask a doctor if rash occurs

When using this product, keep out of eyes. Rinse with water to remove.

KEEP OUT OF REACH OF CHILDREN

Keep out of reach of the children. If product is swallowed, get medical help or contact a poison control center right away.

INACTIVE INGREDIENT

Water, Butyloctyl Salicylate, Niacinamide, Dicaprylyl Carbonate, Dipropylene Glycol, Cetearyl Alcohol, Cetearyl Glucoside, Poly C10-30 Alkyl Acrylate, Sorbitan Olivate, Polymethylsilsesquioxane, Vaccinium Angustifolium (Blueberry) Fruit Extract, Benzyl Glycol, Glyceryl Stearate SE, Panthenol, Carbomer, Arginine, Ganoderma Lucidum (Mushroom) Stem Extract, Tocopheryl Acetate, Glycerin, Glyceryl Glucoside, Disodium EDTA, Ethylhexylglycerin, Xanthan Gum, Hydroxypropyl Methylcellulose Stearoxy Ether, Adenosine, Caprylic/Capric Triglyceride, Propanediol, Sodium Hyaluronate Crosspolymer, Hydrogenated lecithin, Hydrolyzed Glycosaminoglycans, 1,2-Hexanediol, Sodium Hyaluronate, Tocopherol, Hydrolyzed Hyaluronic Acid, Phytosterols, Hyaluronic Acid, Fragrance

OTHER SAFETY INFORMATION

Protect the product in this container from excessive heat and direct sun